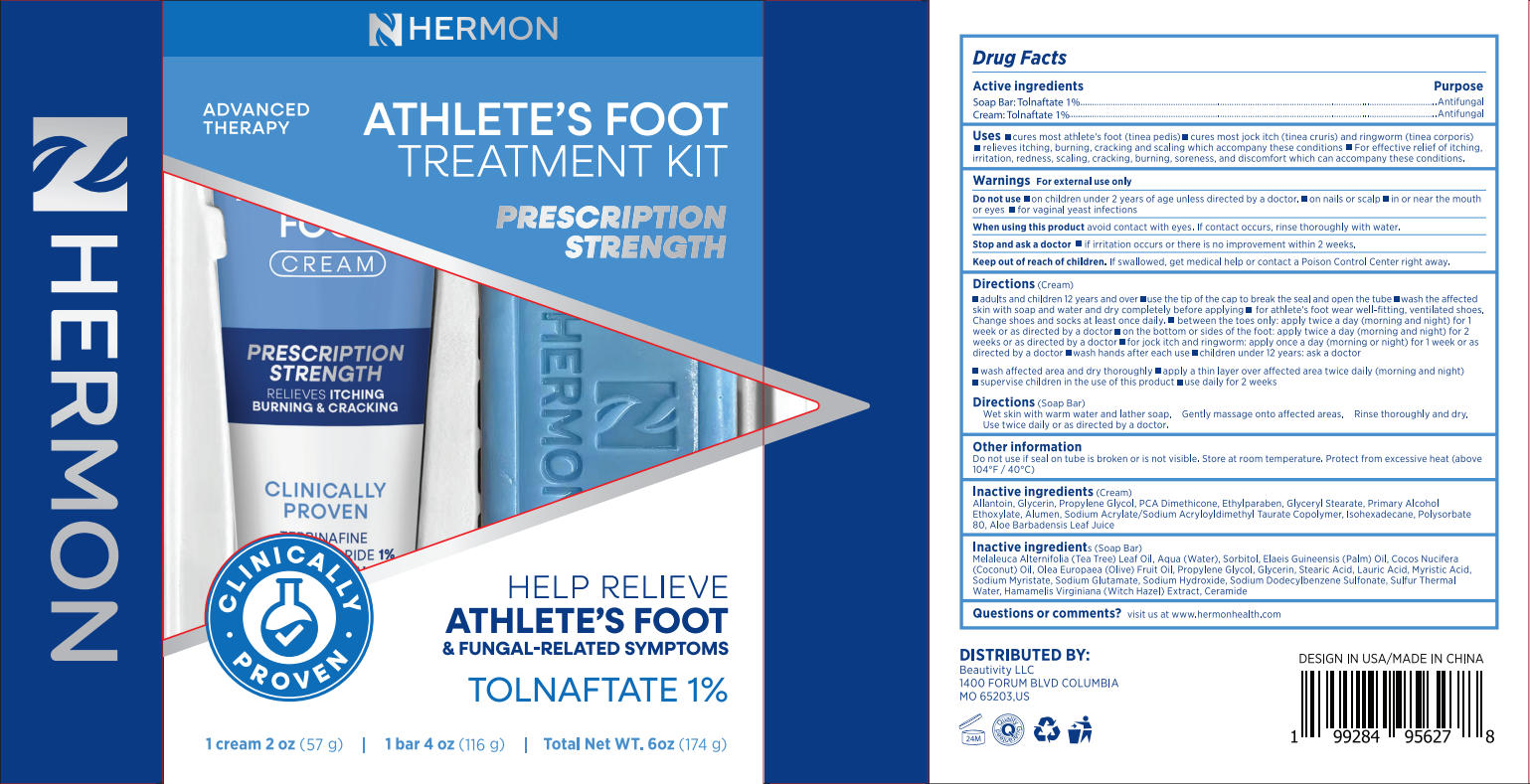 DRUG LABEL: Hermon Athletes foot Tolnaftate 1% kit
NDC: 85398-018 | Form: KIT | Route: TOPICAL
Manufacturer: Beautivity LLC
Category: otc | Type: HUMAN OTC DRUG LABEL
Date: 20251016

ACTIVE INGREDIENTS: TOLNAFTATE 1.16 g/116 g; TOLNAFTATE 0.57 g/57 g
INACTIVE INGREDIENTS: OLEA EUROPAEA (OLIVE) FRUIT OIL; GLYCERIN; ELAEIS GUINEENSIS (PALM) OIL; SODIUM HYDROXIDE; MELALEUCA ALTERNIFOLIA (TEA TREE) LEAF OIL; SULFUR; PROPYLENE GLYCOL; WATER; COCOS NUCIFERA (COCONUT) OIL; STEARIC ACID; SODIUM GLUTAMATE; SODIUM MYRISTATE; MYRISTIC ACID; HAMAMELIS VIRGINIANA BARK; LAURIC ACID; SODIUM DODECYLBENZENESULFONATE; SORBITOL; ALOE VERA LEAF JUICE; ALCOHOL; POLYSORBATE 80; ETHYLPARABEN; GLYCERYL STEARATE; DIMETHICONE 6; GLYCERIN; PROPYLENE GLYCOL; ISOHEXADECANE; HYDROXYETHYL ACRYLATE/SODIUM ACRYLOYLDIMETHYL TAURATE COPOLYMER (45000 MPA.S AT 1%); POTASSIUM ALUM; ALLANTOIN

Initial Drug Listing - Hermon Athlete's foot Tolnaftate 1% kit

ACTIVE INGREDIENT

- Soap Bar: Tolnaftate 1%
- Cream: Tolnaftate 1%

PURPOSE

Antifungal

DOSAGE AND ADMINISTRATION

- cures most athlete's foot (tinea pedis)
- cures most jock itch(tinea cruris) and ringworm (tinea corporis)
- relieves itching, burning, cracking and scaling which accomppany these conditions
- For effective relief of itching, cirritation, redness, scaling, cracking, burning, soreness, anddiscomfort which can accompany these conditions.

WARNINGS

For external use only

DO NOT USE

- on children under 2 years of age unless directed by a doctor.
- On nails or scalp
- in or near the mouth or eyes
- for vaginal yeast infections

WHEN USING

avoid contact with eyes. If contact occurs, rinse thoroughly with water.

ASK DOCTOR

if irritation occurs or there is no improvement within 2 wveeks.

KEEP OUT OF REACH OF CHILDREN

If swallowed, get medical help or contact a Poison Control Center right away.

INDICATIONS AND USAGE

Directions (Cream)

- adults and children 12 years and over
- use the tip of thecap to break the seal and open the tube
- wash the affedted skin with soap and water and dry completely before applying
- for athlete's foot wear well-fitting, ventilated shoes. Change shoes and socks at least once daily.
- between the ttoes only: apply twice a day (morning and night) for 1 week or as directed by a doctor
- on the bottom or sides ofthe foot: apply twice a day (morning and night) for 2 weeks or as directed by a doctor
- for jock itch and ringworm: apply oncea day (morning or night) for 1 week or as directed by a doctor
- wash hands after each use
- children under 12 years: ask a doctor
- wash affected area and dry thoroughly
- apply a thin layer over affected area twice daily (morning and night)
- supervise children in the use of this product
- use daily for2 weeks

Directions (Soap Bar)

- Wet skin with warm water and lather soap.
- Gently massage onto affeected areas.
- Rinse thoroughly and dry.
- Use twice daily or as directed by a doctor.

Do not use if seal on tube is broken or is not visible. Store at room temperature. Protect from excessive heat(above 104°F/40°C)

INACTIVE INGREDIENT

Cream:

Allantoin, Glycerin, Propylene Glycol, PCA Dimethicone, Ethylparaben, Glyc Ethoxylate, Alumen, Sodium Acrylate/Sodium Acryloyldimethyl Taurrate Copolymer, Isohexadecane, Polysorbate 80, Aloe Barbadensis Leaf Juice

Soap Bar:

Melaleuca Alternifolia (Tea Tree) Leaf Oil, Aqua (Water), Sorlbitol, Elaeis Guineensis (Palm) Oil, Cocos Nucifera (Coconut) Oil, Olea Europaea (Olive) Fruit Oil, Propylene Glycol, Glyceerin, Stearic Acid, Lauric Acid, Myristic Acid, Šodium Myristate, Sodium Glutamate, Sodium Hydroxide, Sodium Dodecylbenzene Sulfonate, Sulfur Thermal Water, Hamamelis Virginiana (Witch Hazel) Extract, Ceramide

QUESTIONS

visit us at www.hermonhealth.com